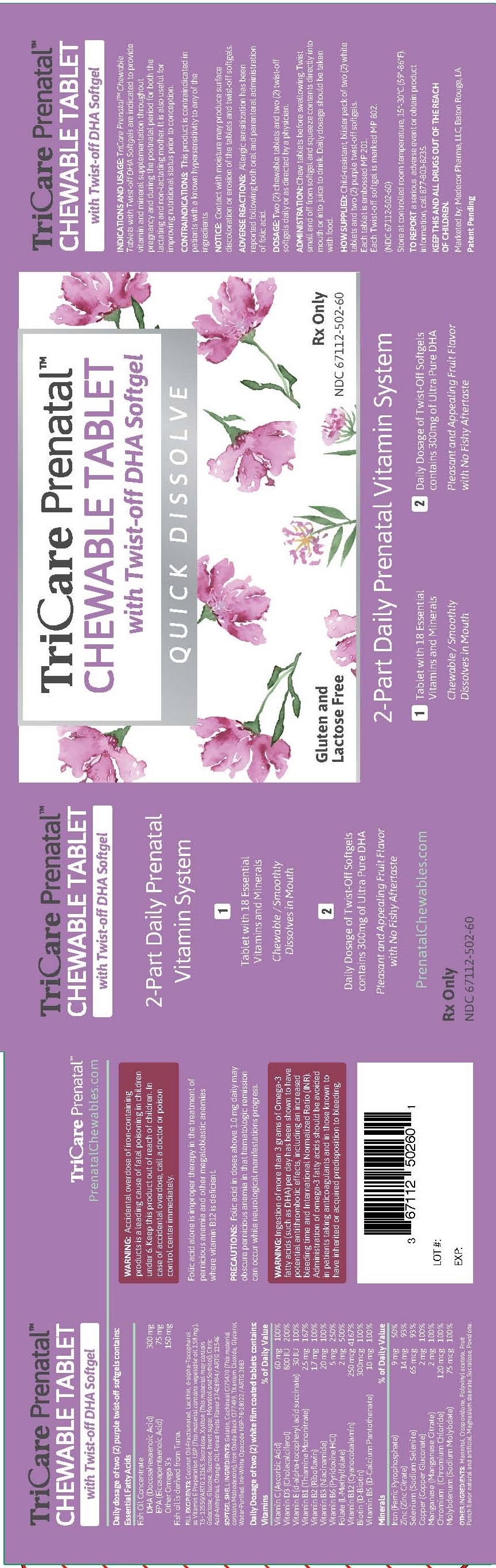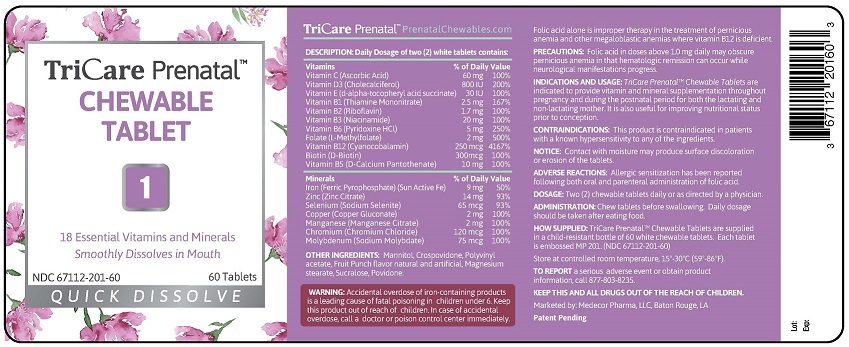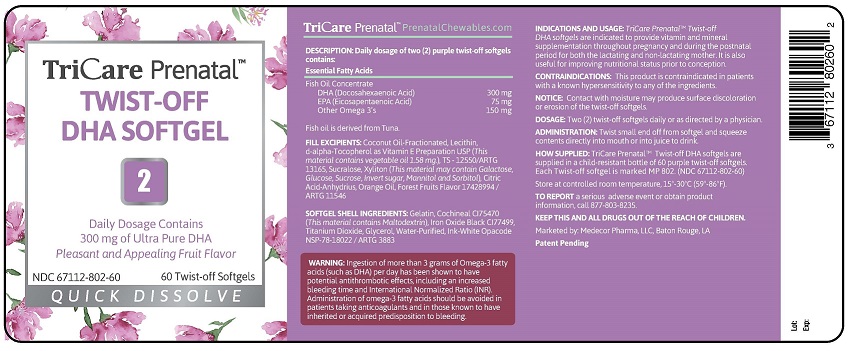 DRUG LABEL: TRICARE PRENATAL 2-PART DAILY PRENATAL VITAMIN SYSTEM
NDC: 67112-502 | Form: KIT | Route: ORAL
Manufacturer: Medecor Pharma, LLC
Category: prescription | Type: HUMAN PRESCRIPTION DRUG LABEL
Date: 20201113

ACTIVE INGREDIENTS: DOCONEXENT 150 1/1 1; ICOSAPENT 37.5 1/1 1; OMEGA-3 FATTY ACIDS 75 1/1 1; ASCORBIC ACID 30 mg/1 1; CHOLECALCIFEROL 400 [iU]/1 1; .ALPHA.-TOCOPHEROL SUCCINATE, D- 15 [iU]/1 1; THIAMINE MONONITRATE 1.25 mg/1 1; RIBOFLAVIN .85 mg/1 1; NIACINAMIDE 10 mg/1 1; PYRIDOXINE HYDROCHLORIDE 2.5 mg/1 1; LEVOMEFOLIC ACID 1 mg/1 1; CYANOCOBALAMIN .125 mg/1 1; BIOTIN .150 mg/1 1; CALCIUM PANTOTHENATE 5 mg/1 1; FERRIC PYROPHOSPHATE 4.5 mg/1 1; ZINC 7 mg/1 1; SODIUM SELENITE .0325 mg/1 1; COPPER GLUCONATE 1 mg/1 1; MANGANESE CITRATE DECAHYDRATE 1 mg/1 1; CHROMIC CHLORIDE CR-51 .060 mg/1 1; SODIUM MOLYBDATE .0375 mg/1 1
INACTIVE INGREDIENTS: GELATIN; COCHINEAL; FERROSOFERRIC OXIDE; TITANIUM DIOXIDE; GLYCERIN; WATER; COCONUT OIL; LECITHIN, SOYBEAN; TOCOPHEROL; SUCRALOSE; XYLITOL; ANHYDROUS CITRIC ACID; ORANGE OIL; MANNITOL; CROSPOVIDONE; POLYVINYL ACETATE; MAGNESIUM STEARATE; SUCRALOSE; POVIDONE

TRICARE PRENATAL 2-PART DAILY PRENATAL VITAMIN SYSTEM

STATEMENT OF IDENTITY

INDICATIONS AND USAGE: TriCare Prenatal™ Chewable
Tablets with Twist-off DHA Softgels are indicated to provide
vitamin and mineral supplementation throughout
pregnancy and during the postnatal period for both the
lactating and non-lactating mother. It is also useful for
improving nutritional status prior to conception.
CONTRAINDICATIONS: This product is contraindicated in
patients with a known hypersensitivity to any of the
ingredients.
NOTICE: Contact with moisture may produce surface
discoloration or erosion of the tablets and twist-off softgels.
ADVERSE REACTIONS: Allergic sensitization has been
reported following both oral and parenteral administration
of folic acid.
DOSAGE: Two (2) chewable tablets and two (2) twist-off
softgels daily or as directed by a physician.
ADMINISTRATION: Chew tablets before swallowing. Twist
small end off from softgel and squeeze contents directly into
mouth or into juice to drink. Daily dosage should be taken
with food.
HOW SUPPLIED: Child-resistant, blister pack of two (2) white
tablets and two (2) purple twist-off softgels.
Each tablet is embossed MP 201.
Each Twist-off softgel is marked MP 802.
(NDC 67112-502-60)
Store at controlled room temperature, 15º-30ºC (59º-86ºF).
TO REPORT a serious adverse event or obtain product
information, call 877-803-8235.
KEEP THIS AND ALL DRUGS OUT OF THE REACH
OF CHILDREN.
Marketed by: Medecor Pharma, LLC, Baton Rouge, LA
Patent Pending